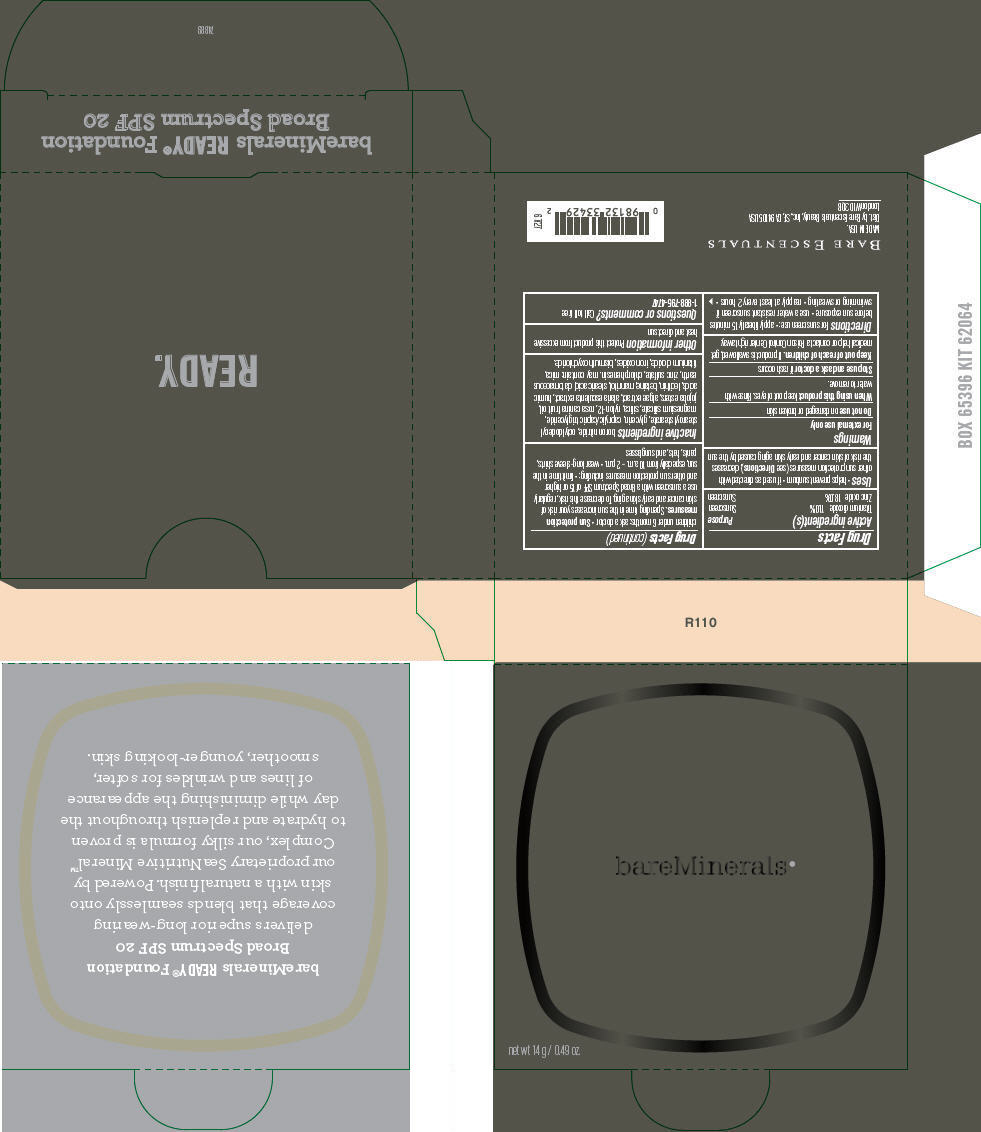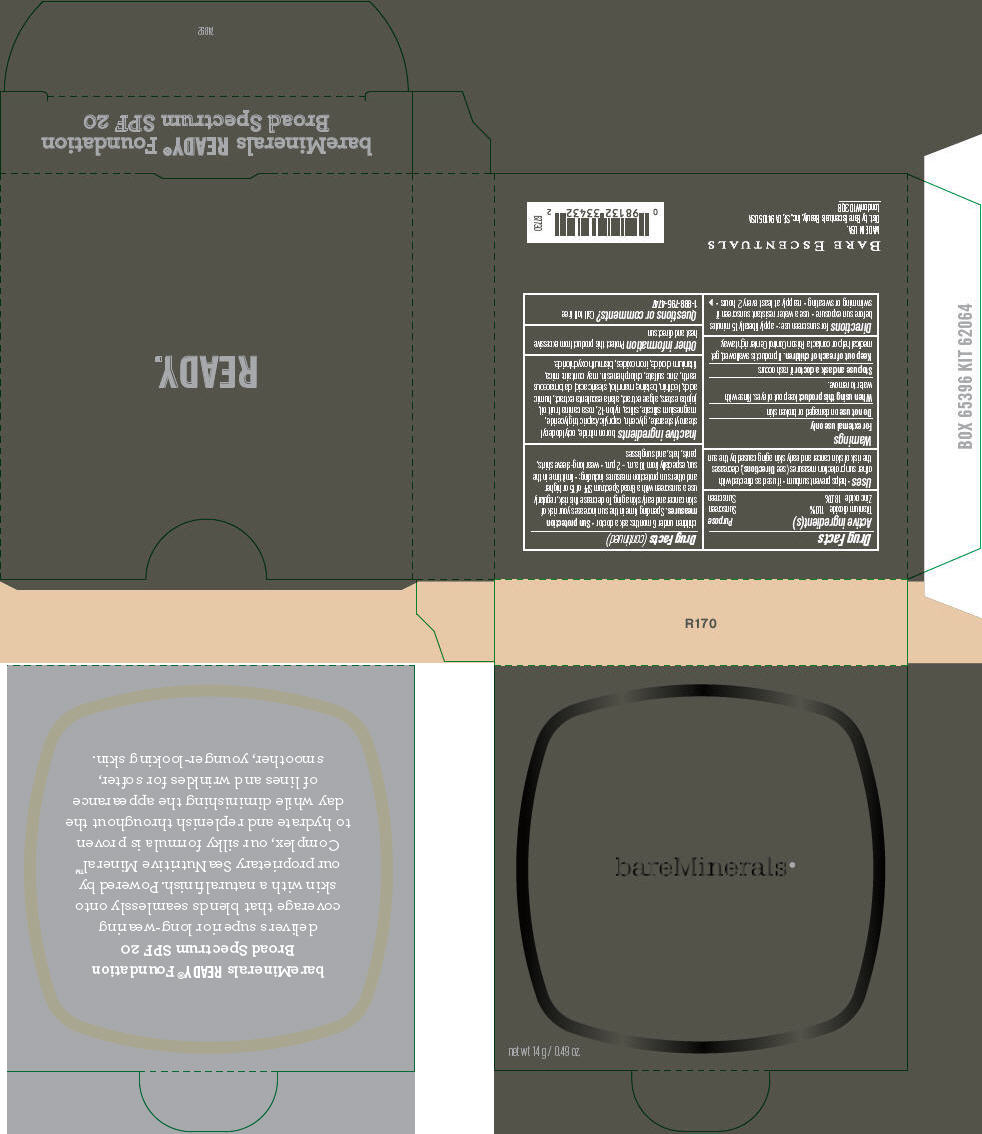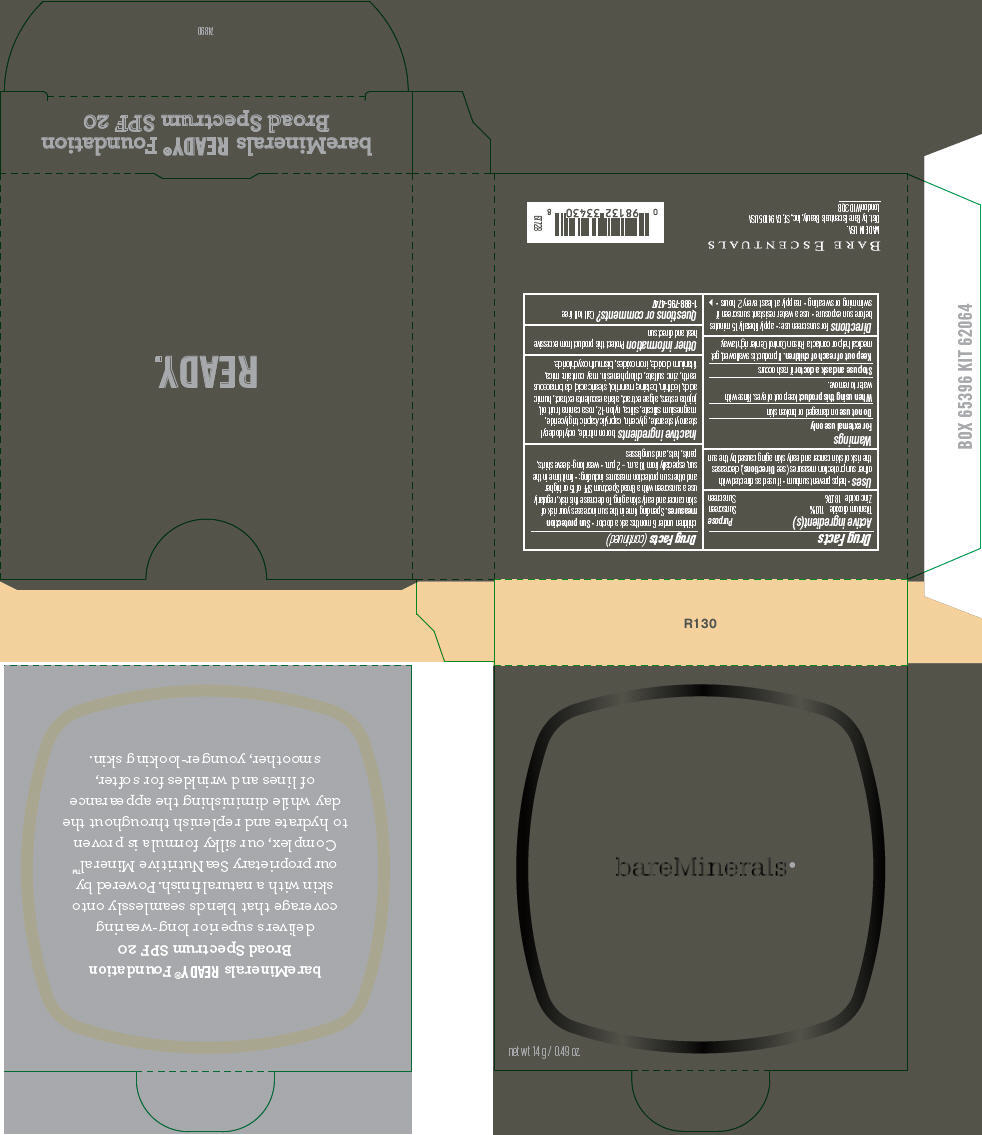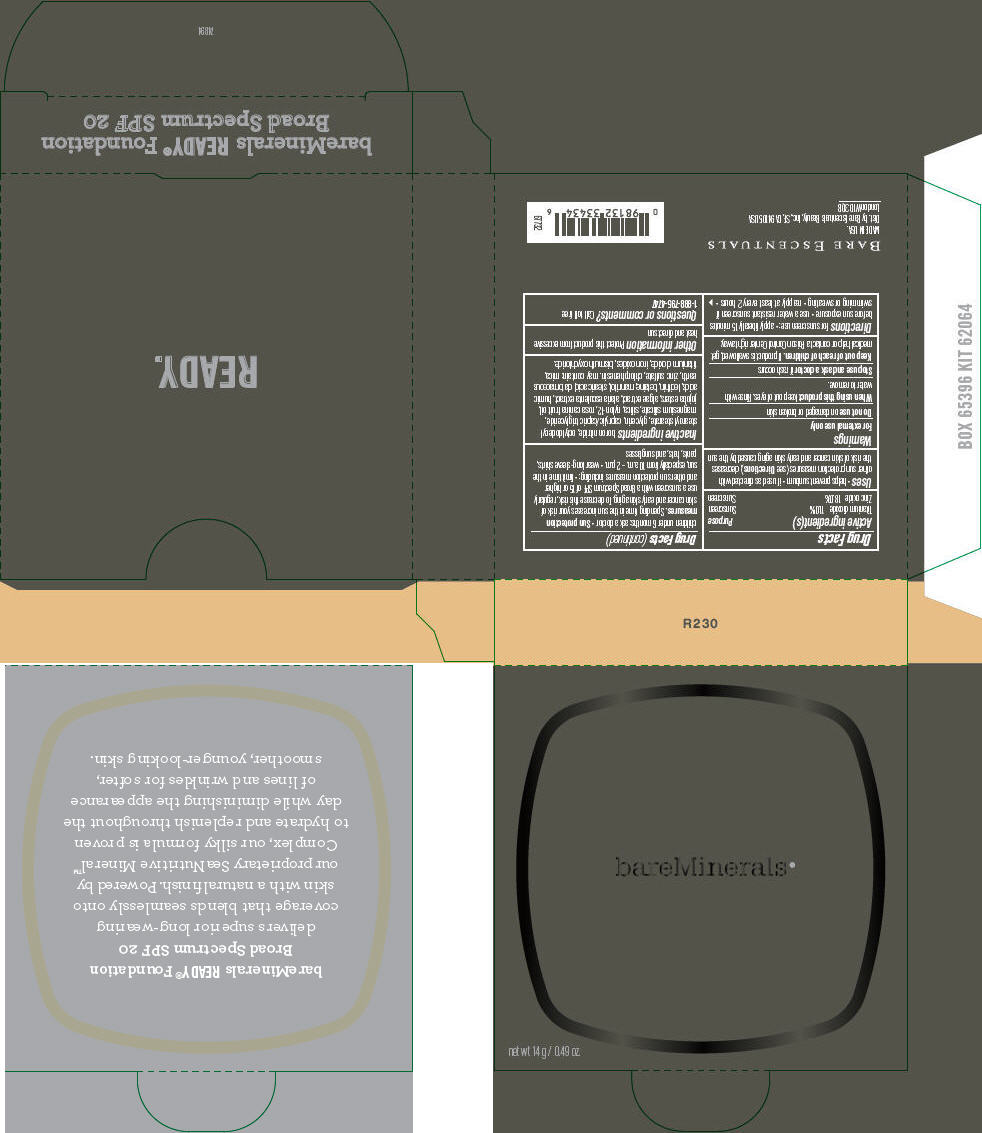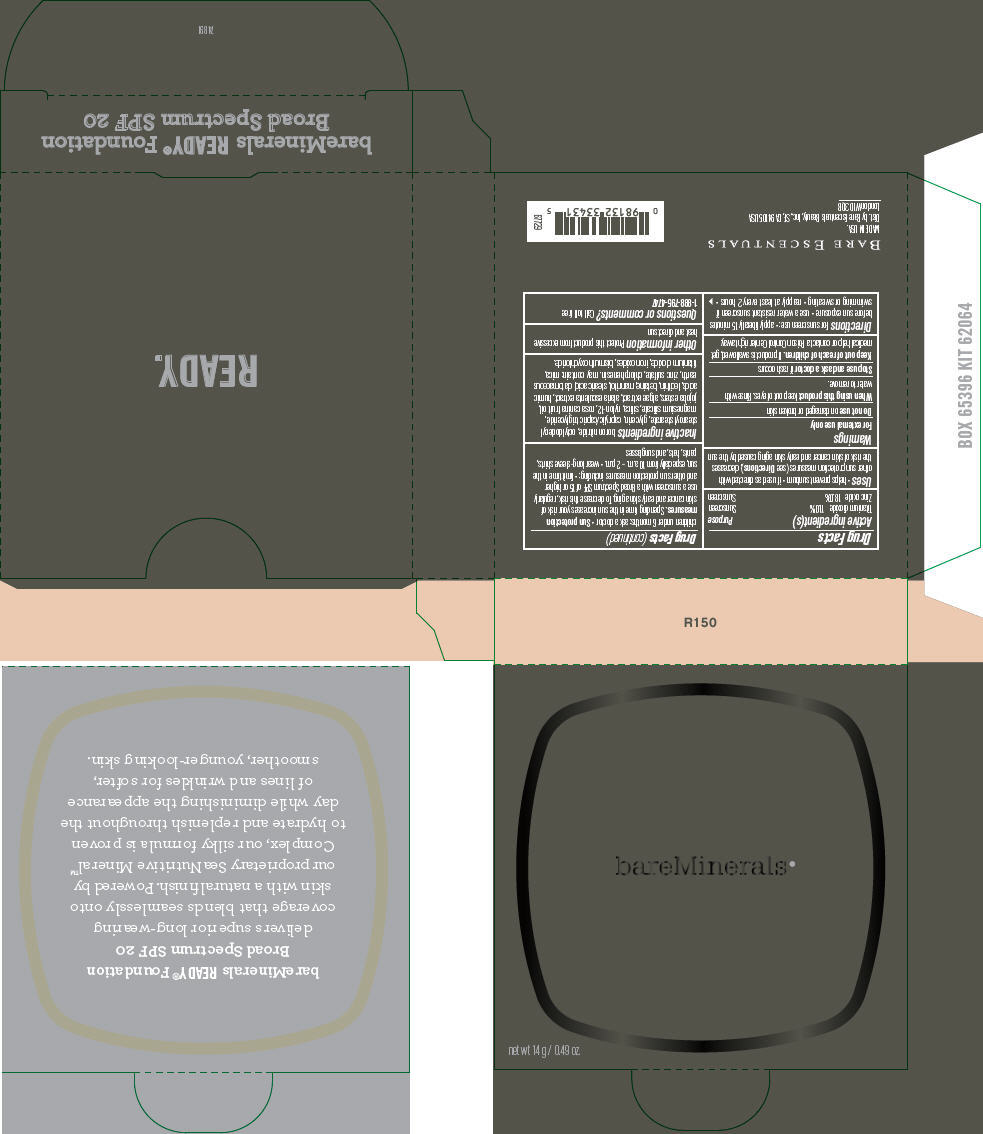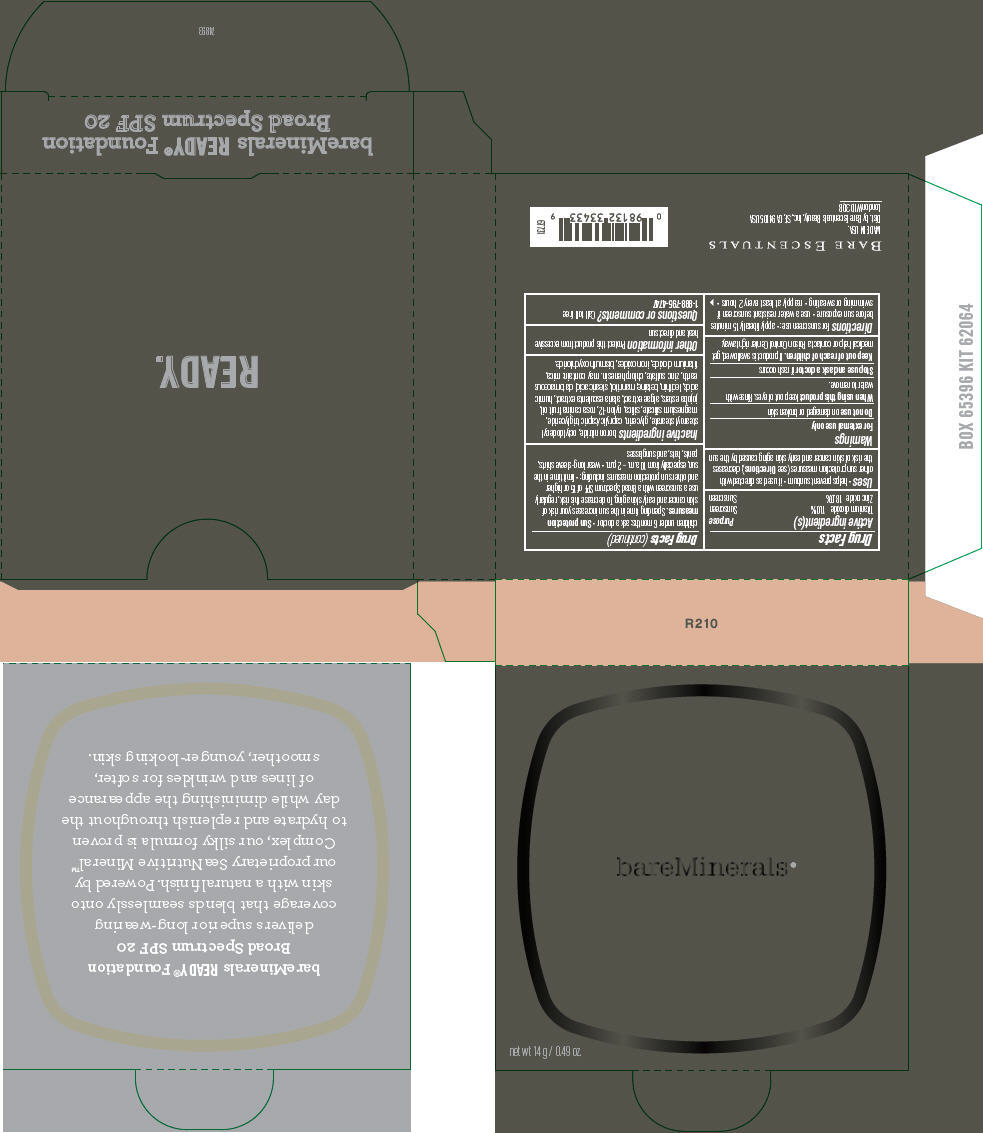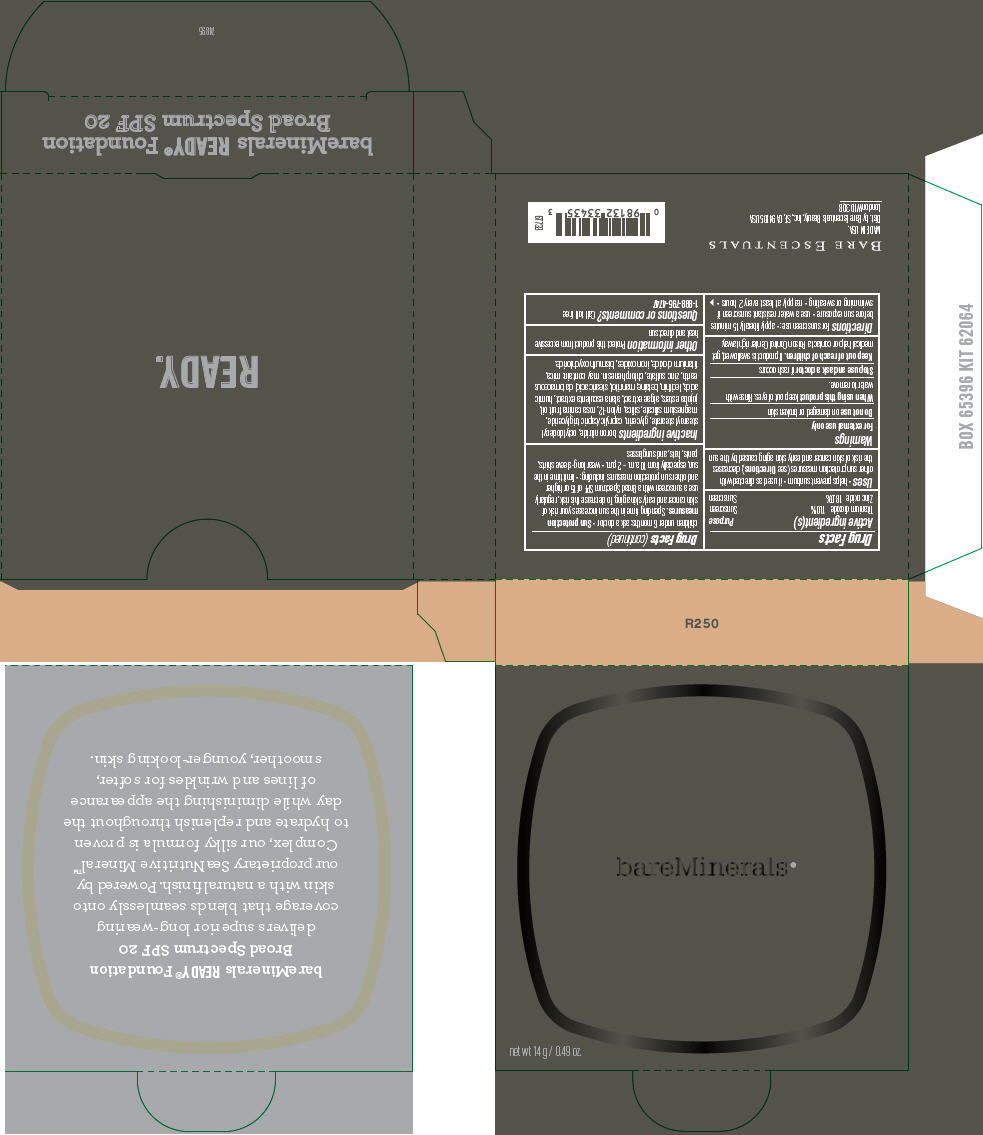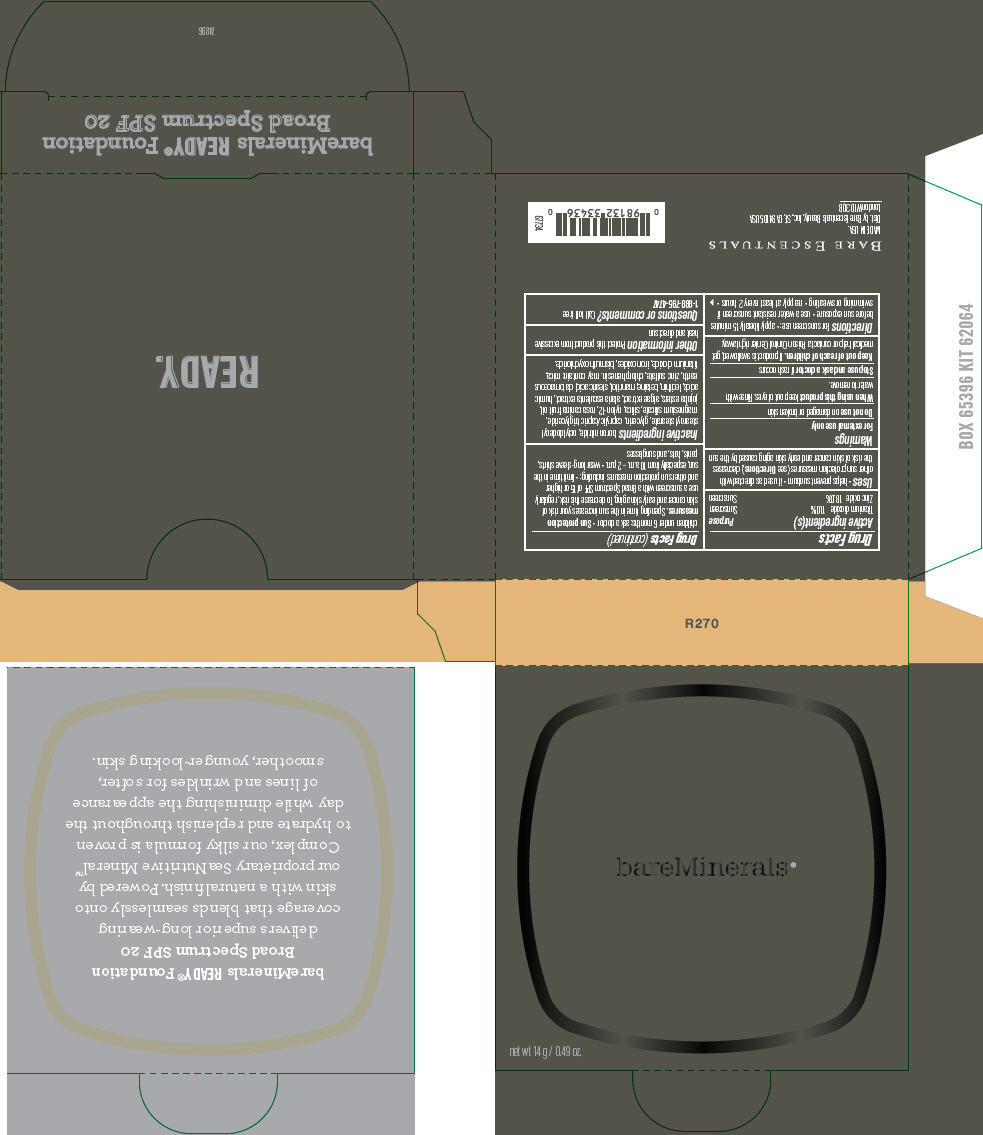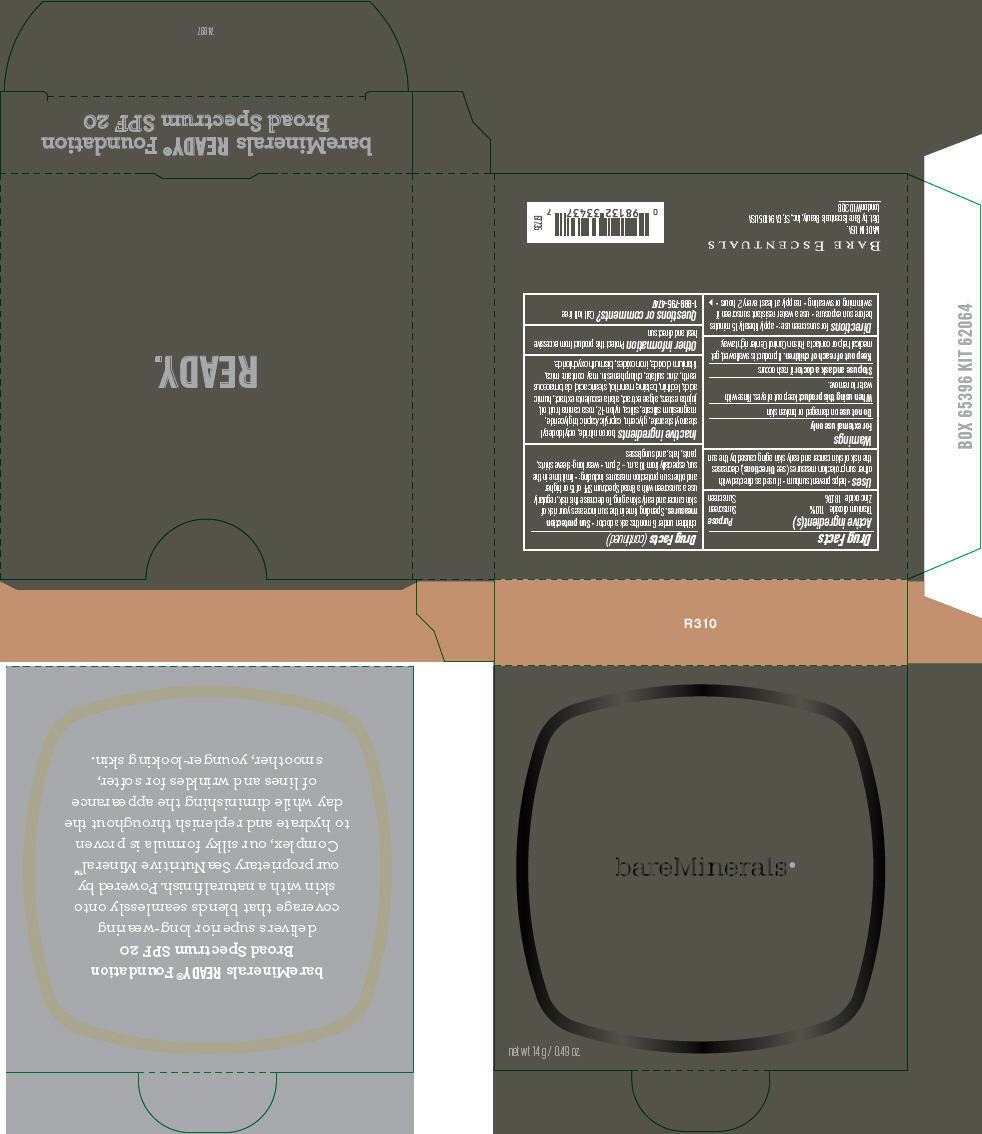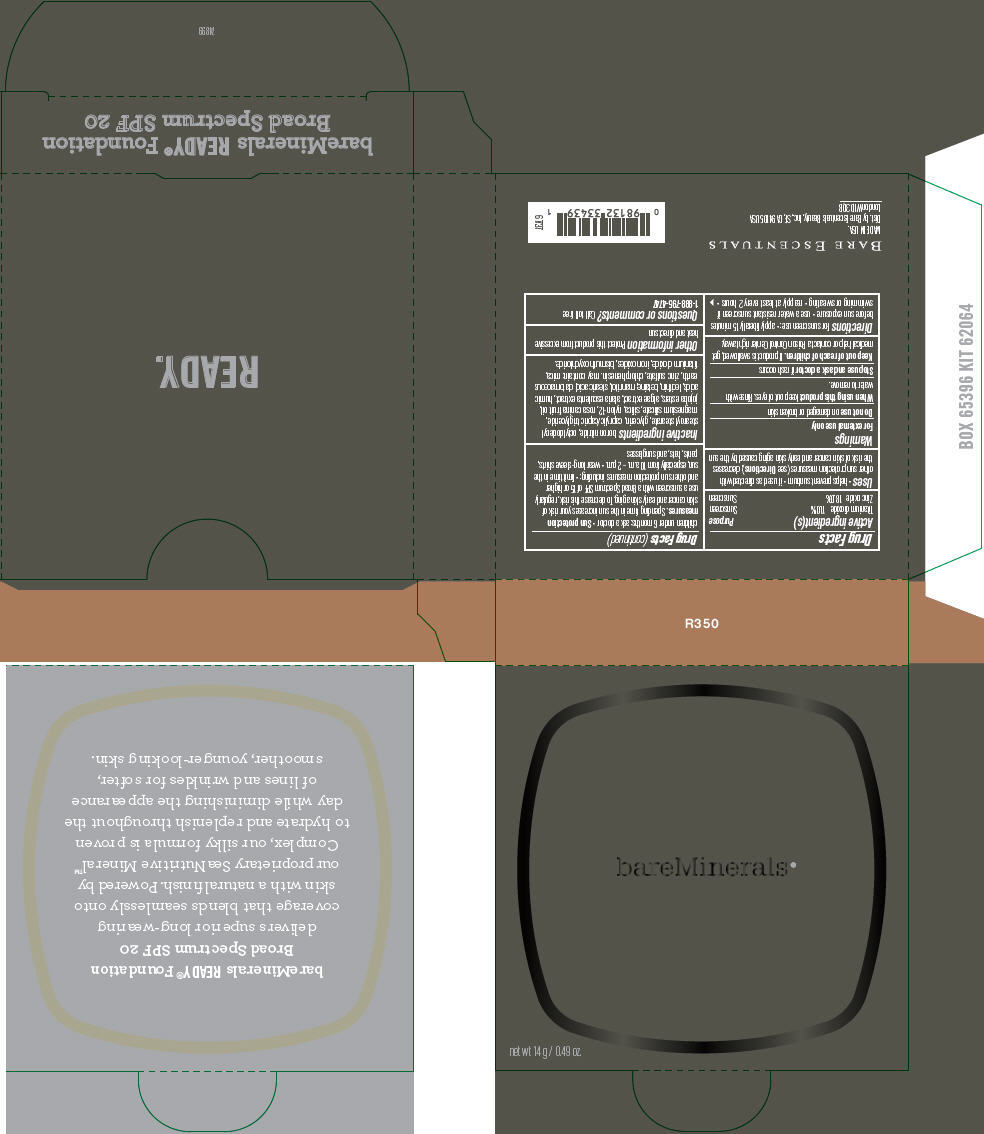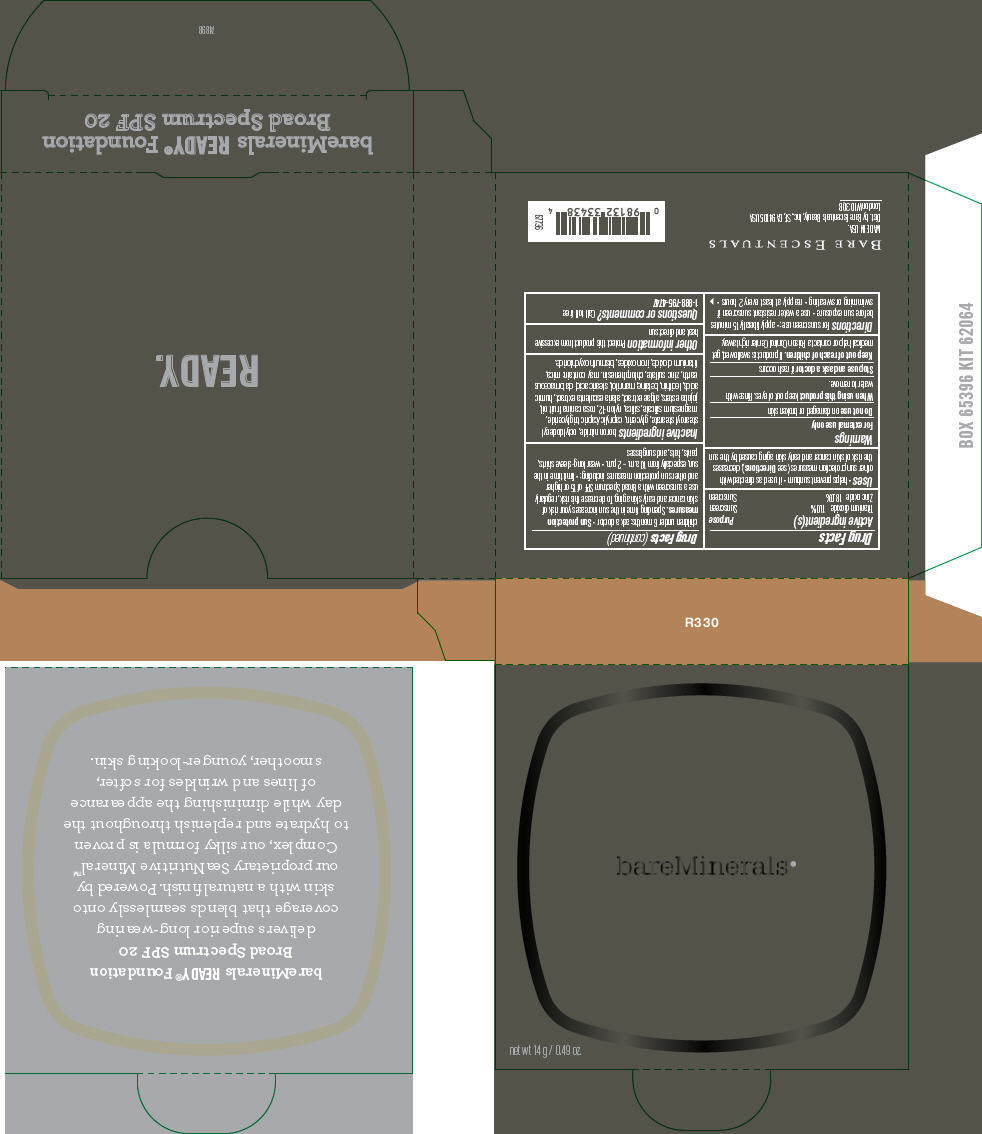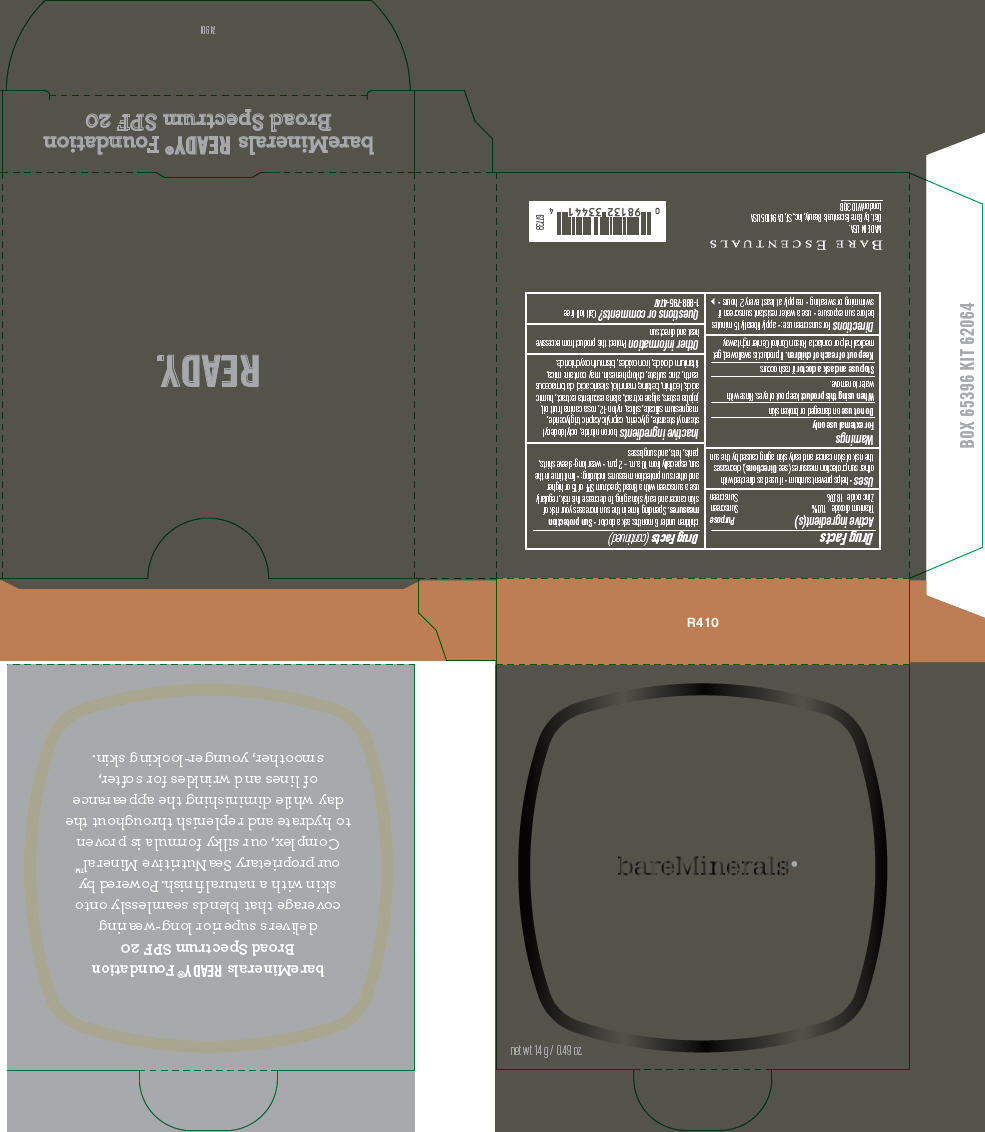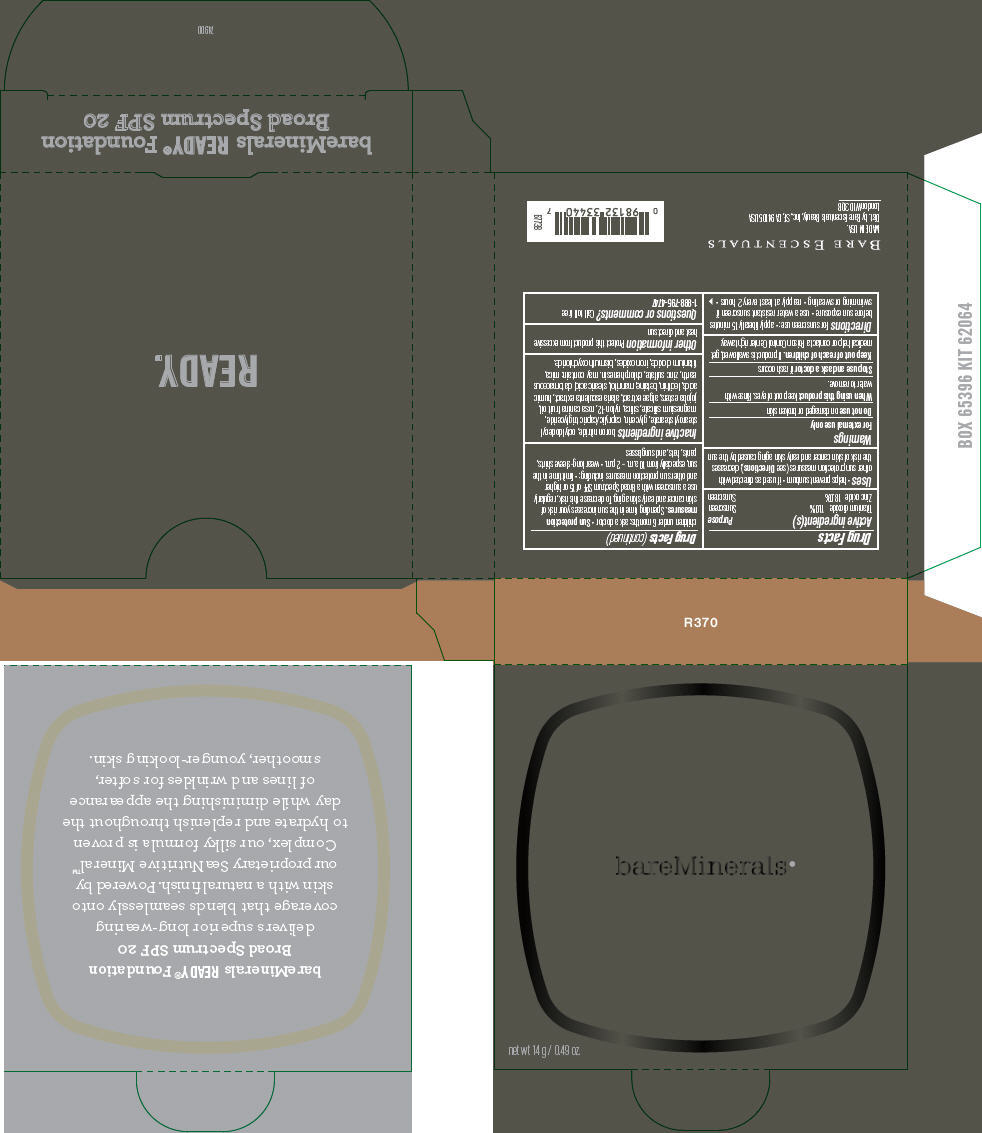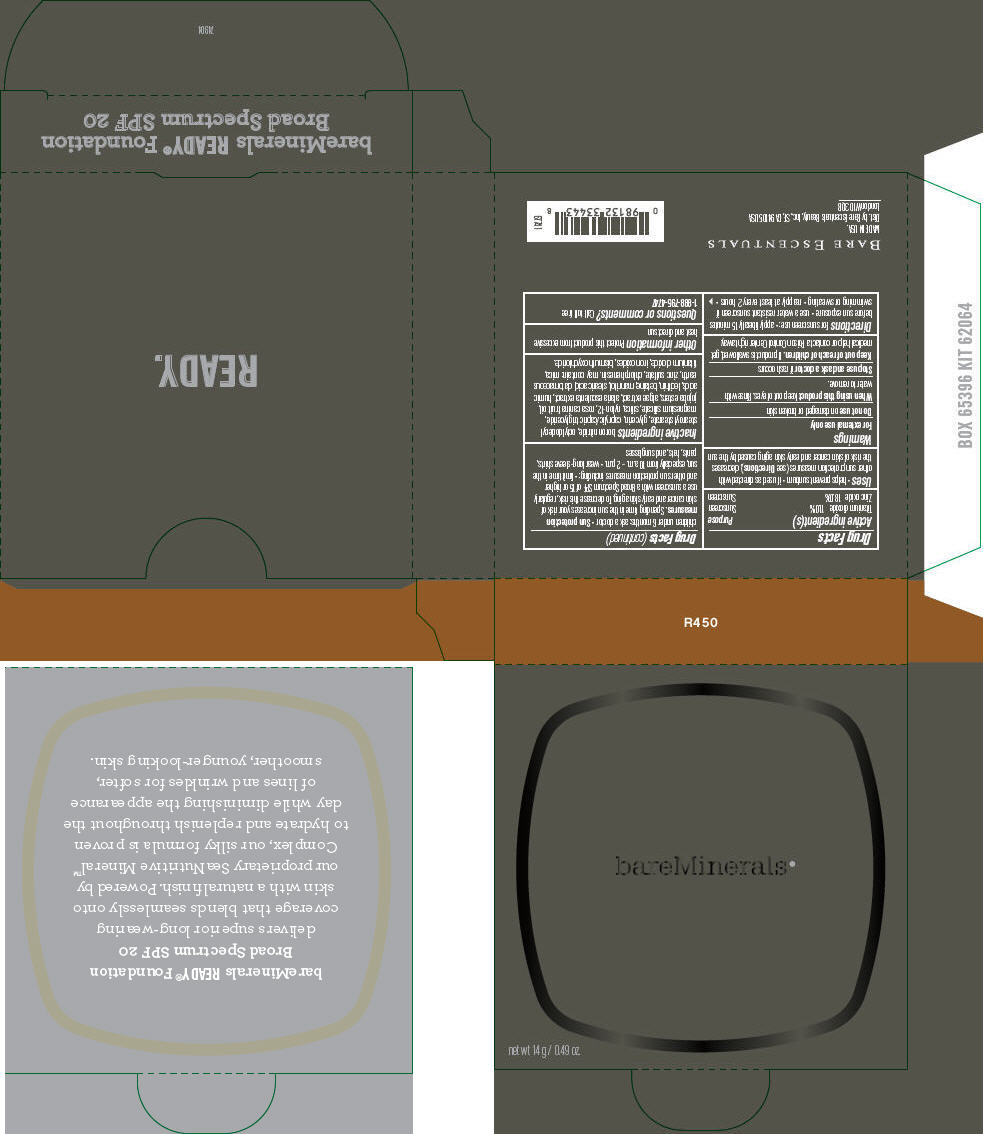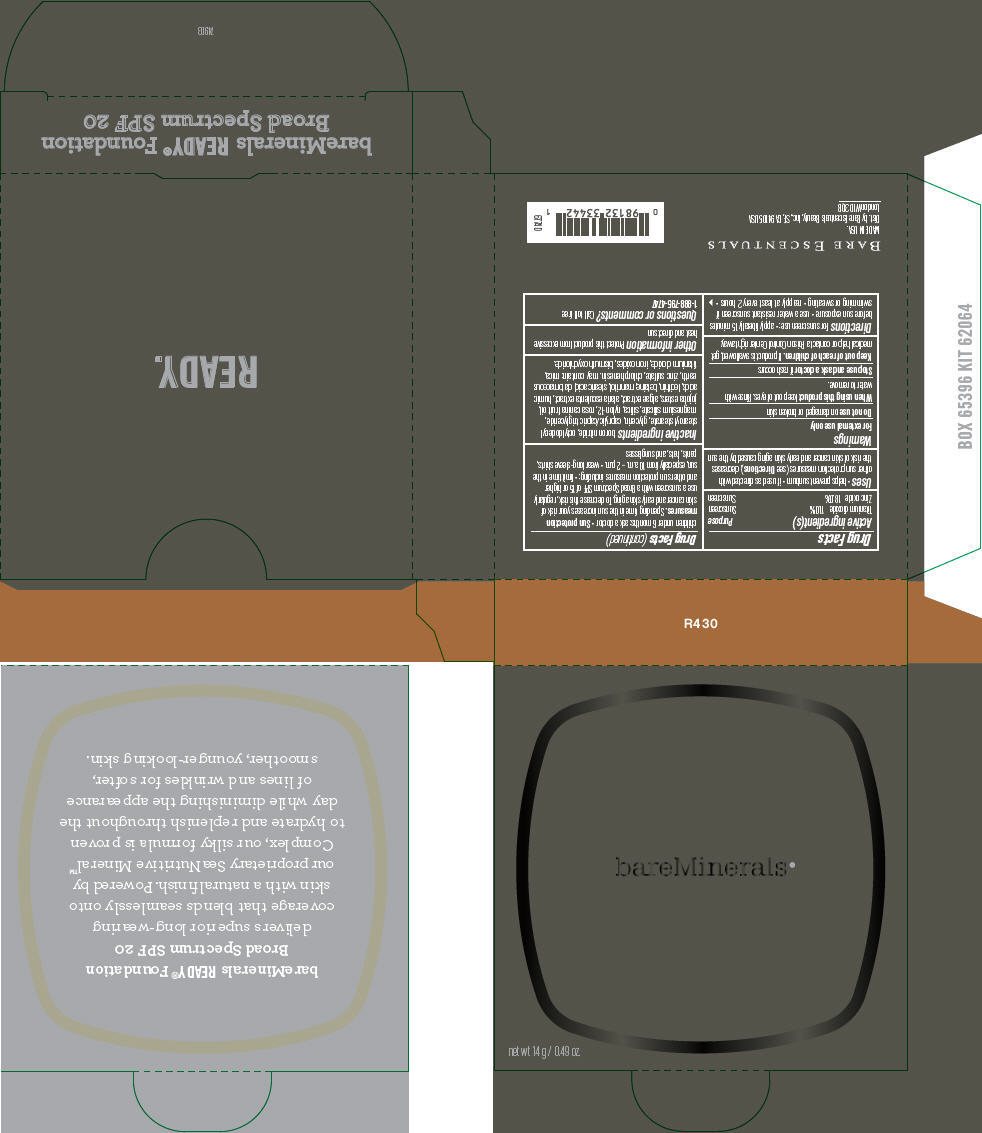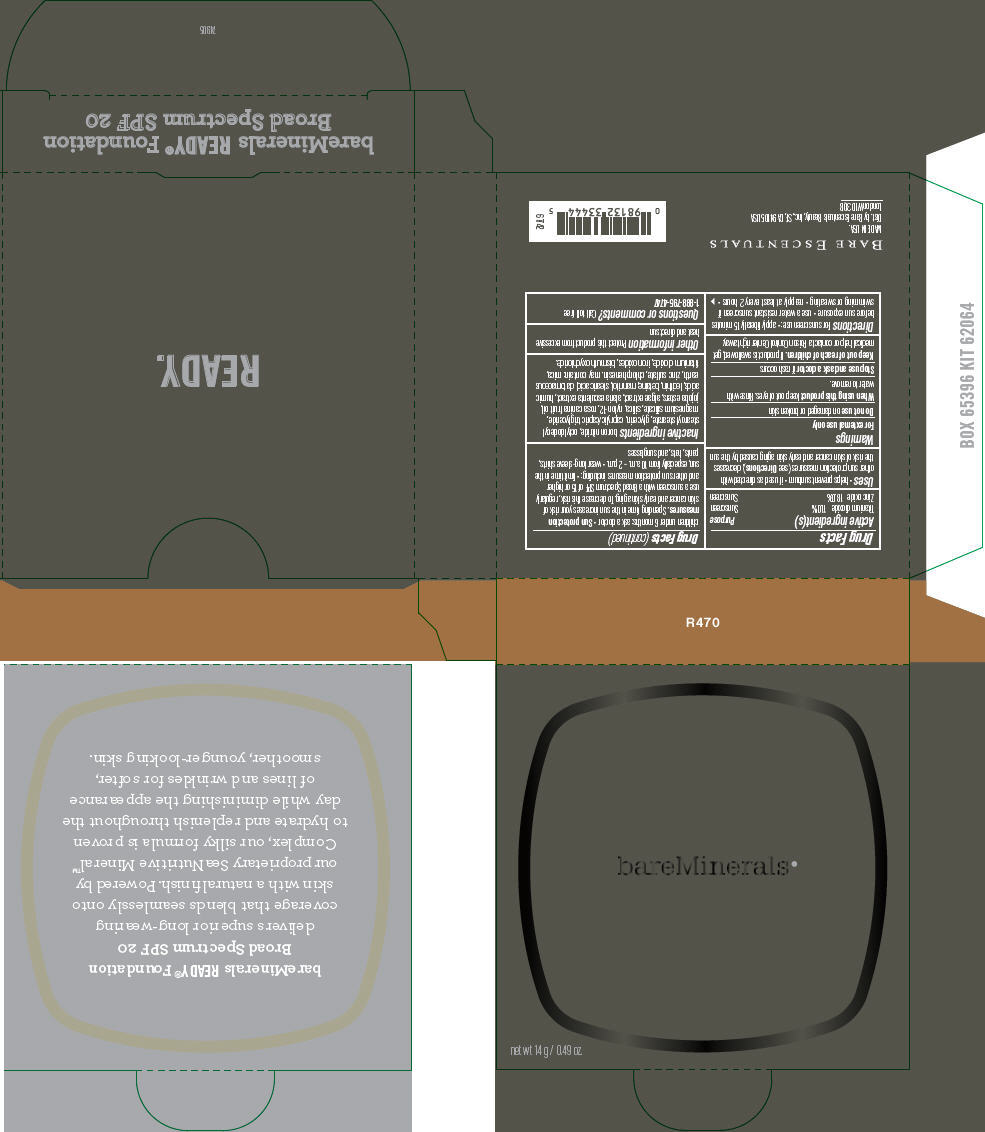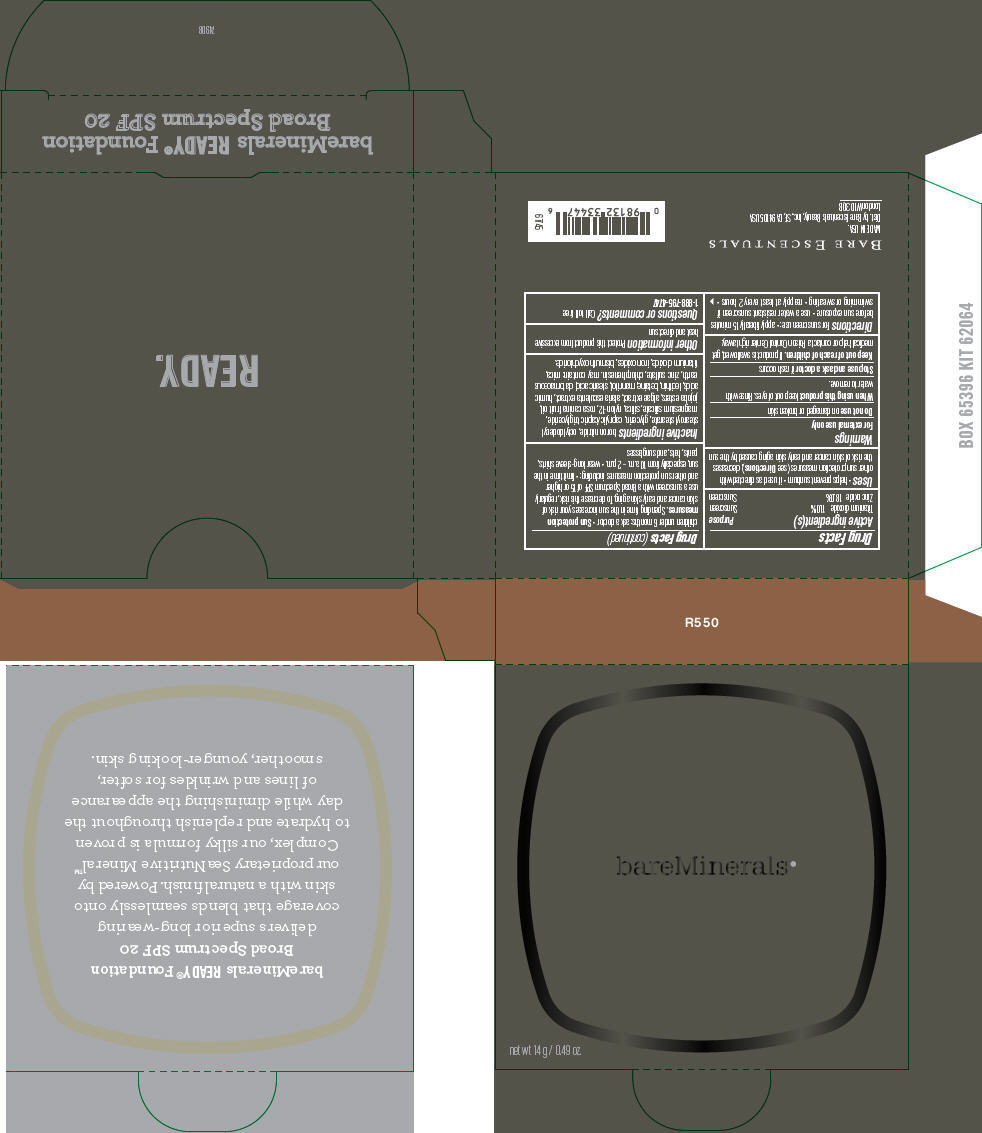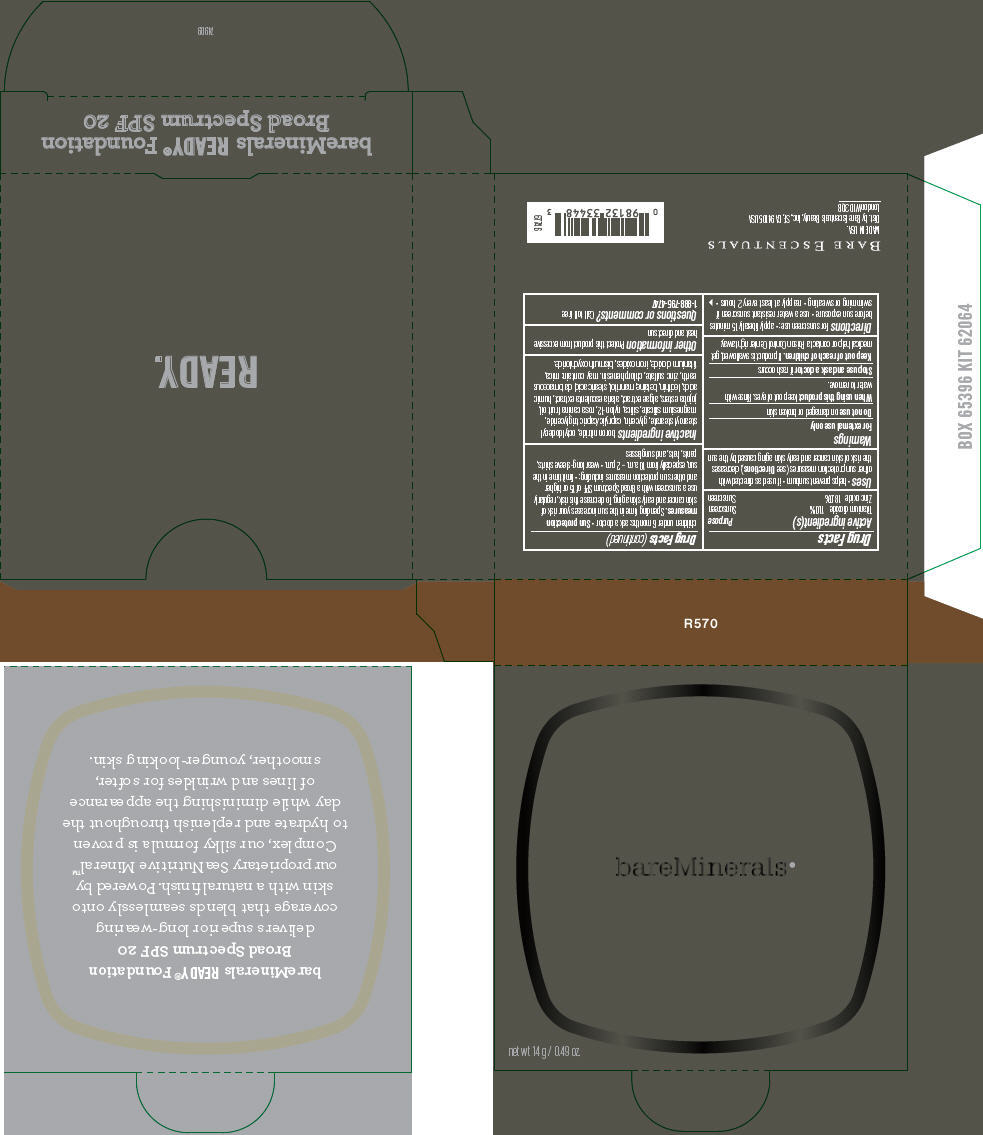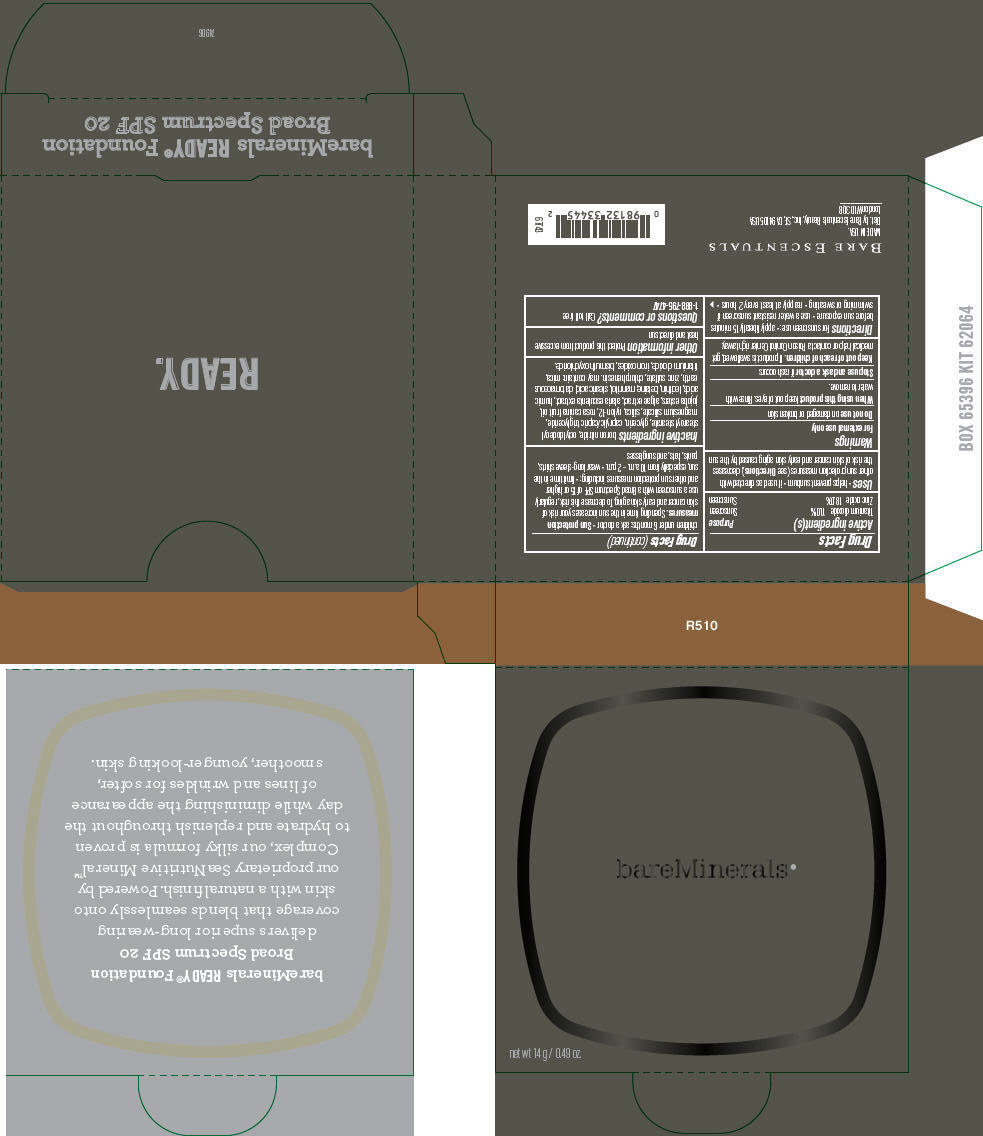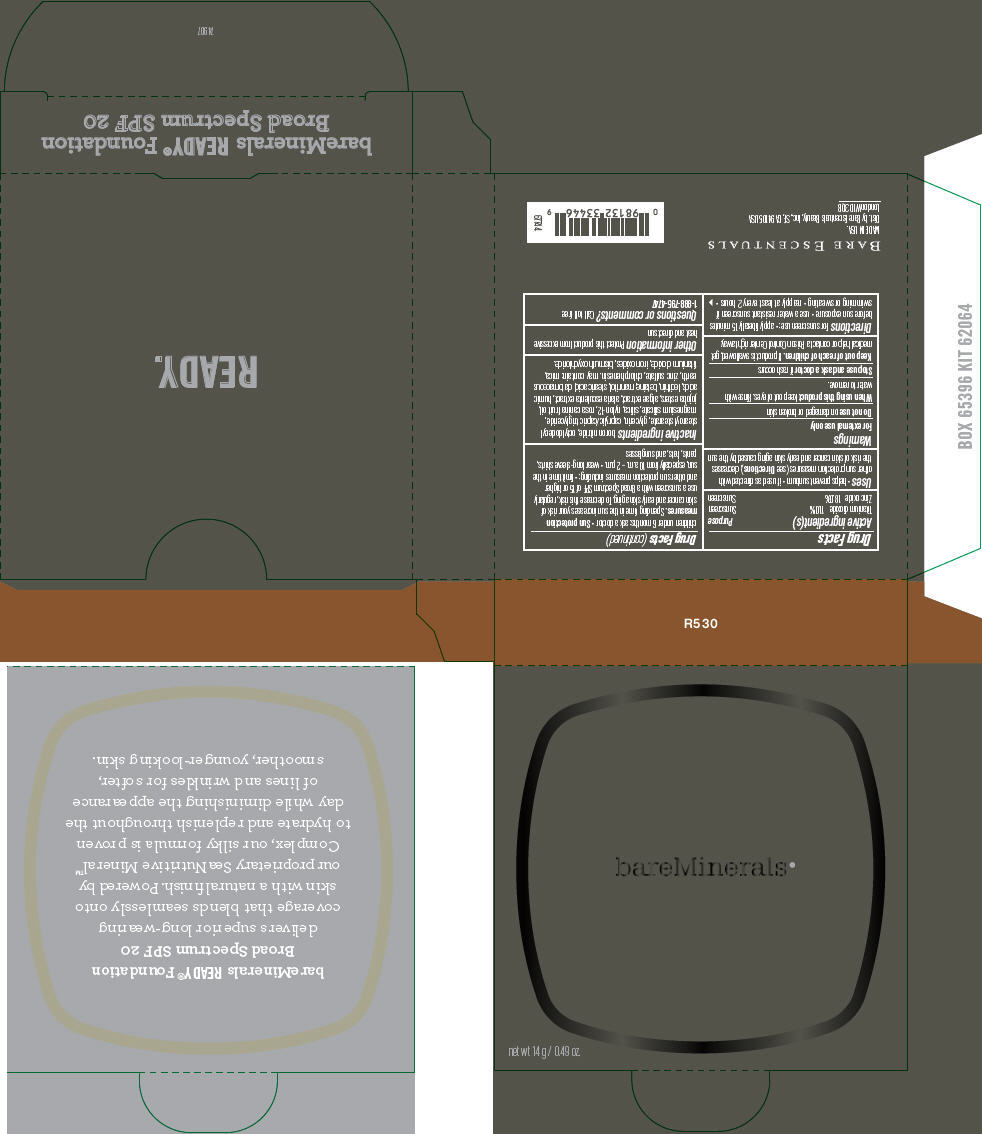 DRUG LABEL: Ready Foundation 
NDC: 98132-163 | Form: POWDER
Manufacturer: Bare Escentuals Beauty Inc.
Category: otc | Type: HUMAN OTC DRUG LABEL
Date: 20141001

ACTIVE INGREDIENTS: Titanium Dioxide 11 g/100 g; Zinc Oxide 18 g/100 g
INACTIVE INGREDIENTS: boron nitride; octyldodecyl stearoyl stearate; glycerin; medium-chain triglycerides; magnesium silicate; silicon dioxide; nylon-12; rosa canina fruit oil; alaria esculenta; betaine; mannitol; stearic acid; diatomaceous earth; zinc sulfate; chlorphenesin; mica; ferric oxide red; bismuth oxychloride

bareMinerals® Ready Foundation Broad Spectrum SPF 20

Drug Facts

ACTIVE INGREDIENT

Active ingredient(s) | Purpose
Titanium dioxide 11.0% | Sunscreen
Zinc oxide 18.0% | Sunscreen

Uses

- helps prevent sunburn
- if used as directed with other sun protection measures (see Directions), decreases the risk of skin cancer and early skin aging caused by the sun

Warnings

For external use only

Do not use on damaged or broken skin

When using this product keep out of eyes. Rinse with water to remove.

Stop use and ask a doctor if rash occurs

Keep out of reach of children. If product is swallowed, get medical help or contact a Poison Control Center right away.

Directions

For sunscreen use:

- apply liberally 15 minutes before sun exposure
- use a water resistant sunscreen if swimming or sweating
- reapply at least every 2 hours
- children under 6 months: ask a doctor
- Sun protection measures. Spending time in the sun increases your risk of skin cancer and early skin aging. To decrease this risk, regularly use a sunscreen with a Broad Spectrum SPF of 15 or higher and other sun protection measures including:
  - limit time in the sun, especially from 10 a.m. – 2 p.m.
  - wear long-sleeve shirts, pants, hats, and sunglasses

Inactive ingredients

boron nitride, octyldodecyl stearoyl stearate, glycerin, caprylic/capric triglyceride, magnesium silicate, silica, nylon-12, rosa canina fruit oil, jojoba esters, algae extract, alaria esculenta extract, humic acids, lecithin, betaine, mannitol, stearic acid, diatomaceous earth, zinc sulfate, chlorphenesin. may contain: mica, titanium dioxide, iron oxides, bismuth oxychloride.

Other information

Protect this product from excessive heat and direct sun

Questions or comments?

Call toll free 1-888-795-4747

Dist. by Bare Escentuals Beauty, Inc., SF, CA 94105 USA

PRINCIPAL DISPLAY PANEL - 14 g Carton - R110

bareMinerals®

net wt 14 g / 0.49 oz.

PRINCIPAL DISPLAY PANEL - 14 g Carton - R170

bareMinerals®

net wt 14 g / 0.49 oz.

PRINCIPAL DISPLAY PANEL - 14 g Carton - R130

bareMinerals®

net wt 14 g / 0.49 oz.

PRINCIPAL DISPLAY PANEL - 14 g Carton - R230

bareMinerals®

net wt 14 g / 0.49 oz.

PRINCIPAL DISPLAY PANEL - 14 g Carton - R150

bareMinerals®

net wt 14 g / 0.49 oz.

PRINCIPAL DISPLAY PANEL - 14 g Carton - R210

bareMinerals®

net wt 14 g / 0.49 oz.

PRINCIPAL DISPLAY PANEL - 14 g Carton - R250

bareMinerals®

net wt 14 g / 0.49 oz.

PRINCIPAL DISPLAY PANEL - 14 g Carton - R270

bareMinerals®

net wt 14 g / 0.49 oz.

PRINCIPAL DISPLAY PANEL - 14 g Carton - R310

bareMinerals®

net wt 14 g / 0.49 oz.

PRINCIPAL DISPLAY PANEL - 14 g Carton - R350

bareMinerals®

net wt 14 g / 0.49 oz.

PRINCIPAL DISPLAY PANEL - 14 g Carton - R330

bareMinerals®

net wt 14 g / 0.49 oz.

PRINCIPAL DISPLAY PANEL - 14 g Carton - R410

bareMinerals®

net wt 14 g / 0.49 oz.

PRINCIPAL DISPLAY PANEL - 14 g Carton - R370

bareMinerals®

net wt 14 g / 0.49 oz.

PRINCIPAL DISPLAY PANEL - 14 g Carton - R450

bareMinerals®

net wt 14 g / 0.49 oz.

PRINCIPAL DISPLAY PANEL - 14 g Carton - R430

bareMinerals®

net wt 14 g / 0.49 oz.

PRINCIPAL DISPLAY PANEL - 14 g Carton - R470

bareMinerals®

net wt 14 g / 0.49 oz.

PRINCIPAL DISPLAY PANEL - 14 g Carton - R550

bareMinerals®

net wt 14 g / 0.49 oz.

PRINCIPAL DISPLAY PANEL - 14 g Carton - R570

bareMinerals®

net wt 14 g / 0.49 oz.

PRINCIPAL DISPLAY PANEL - 14 g Carton - R510

bareMinerals®

net wt 14 g / 0.49 oz.

PRINCIPAL DISPLAY PANEL - 14 g Carton - R530

bareMinerals®

net wt 14 g / 0.49 oz.